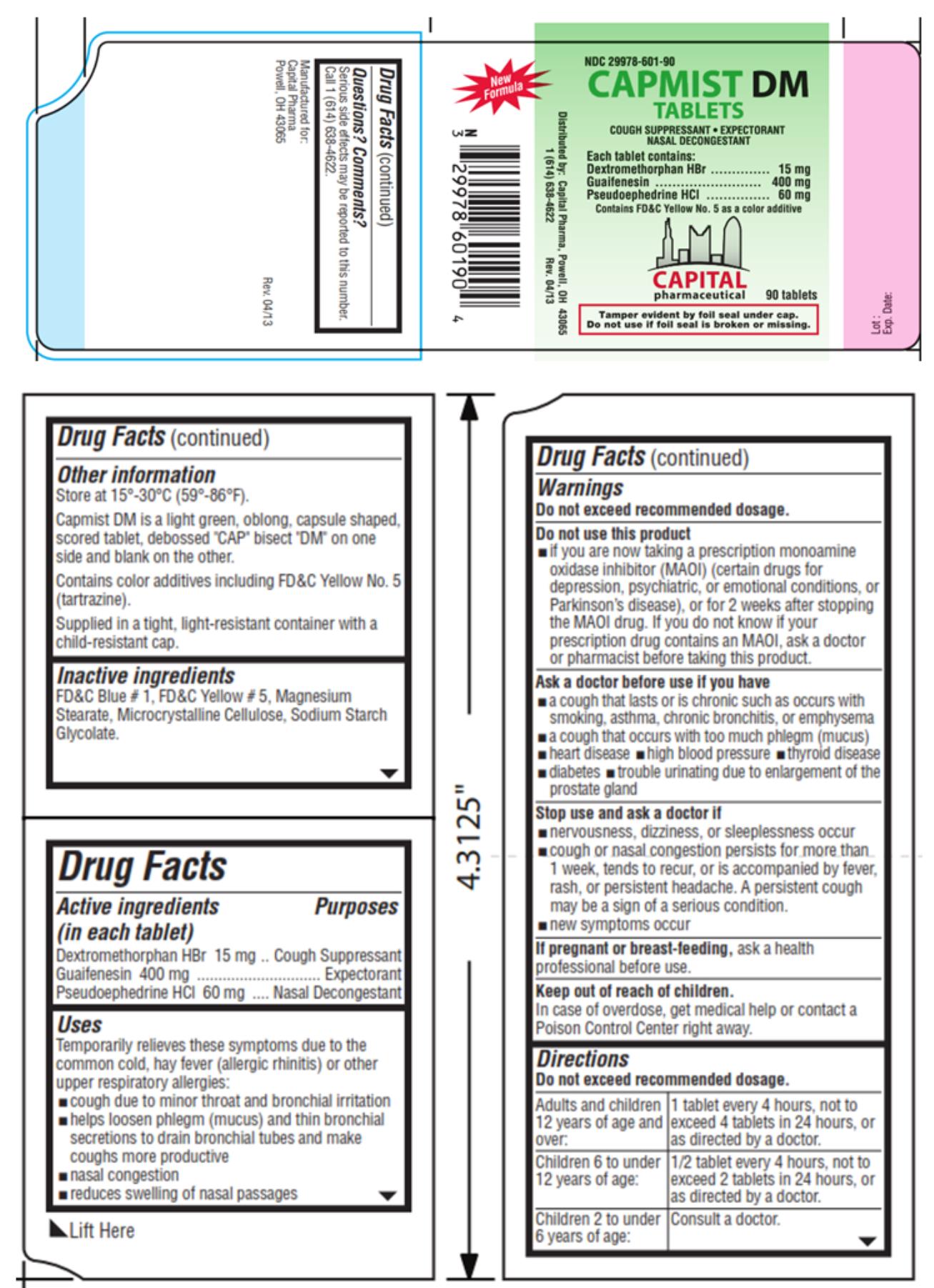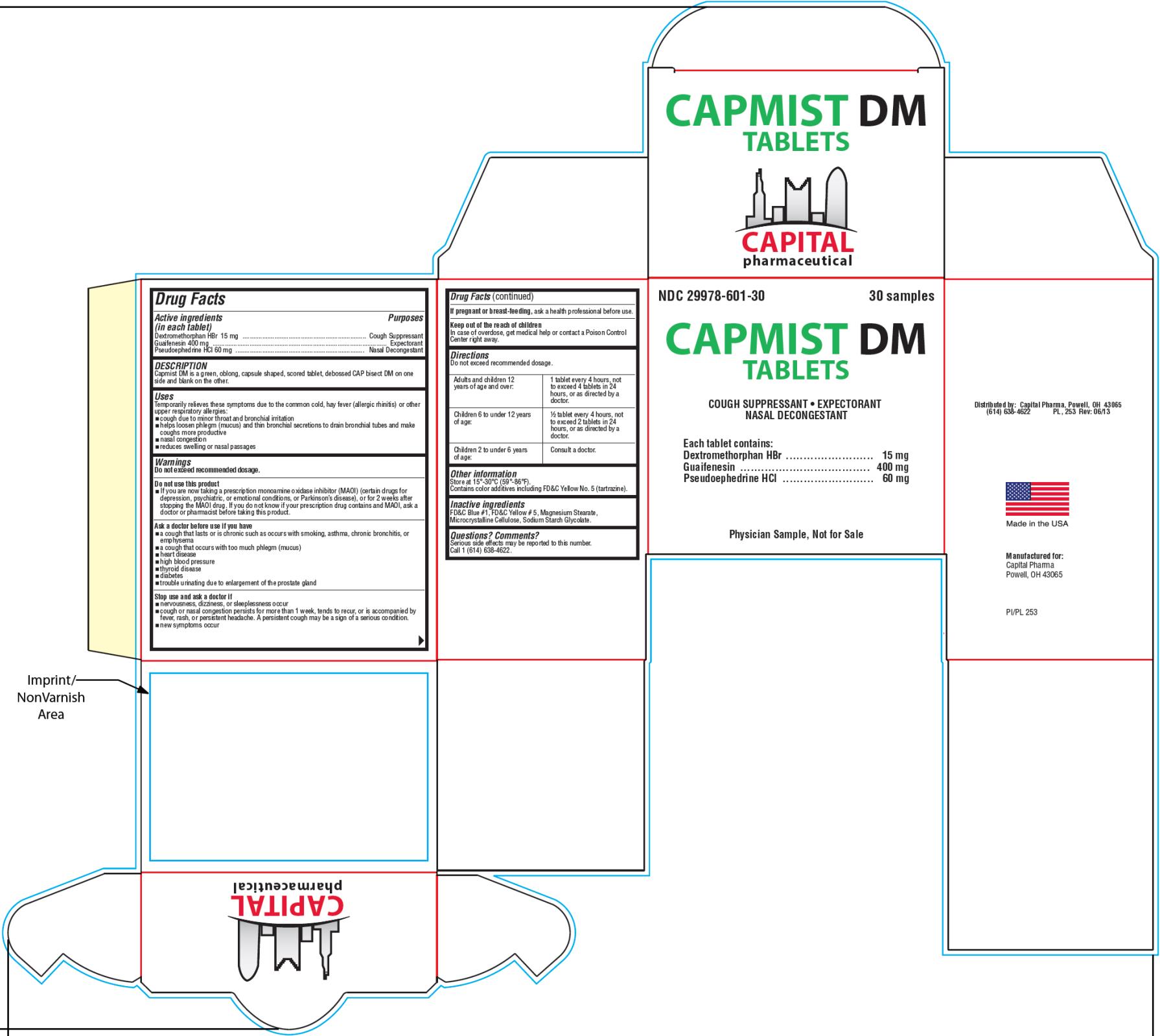 DRUG LABEL: Capmist DM
NDC: 29978-601 | Form: TABLET
Manufacturer: Capital Pharmaceutical, LLC
Category: otc | Type: HUMAN OTC DRUG LABEL
Date: 20251203

ACTIVE INGREDIENTS: DEXTROMETHORPHAN HYDROBROMIDE 15 mg/1 1; GUAIFENESIN 400 mg/1 1; PSEUDOEPHEDRINE HYDROCHLORIDE 60 mg/1 1
INACTIVE INGREDIENTS: FD&C BLUE NO. 1; FD&C YELLOW NO. 5; MAGNESIUM STEARATE; CELLULOSE, MICROCRYSTALLINE; SODIUM STARCH GLYCOLATE TYPE A POTATO

Capmist DM Tablets

Drug Facts

Active ingredients

(in each tablet)

Dextromethorphan HBr 15mg

Purpose

Cough Suppressant

Active ingredients

(in each tablet)

Guaifenesin 400mg

Purpose

Expectorant

Active ingredients

(in each tablet)

Pseudoephedrine HCl 60mg

Purpose

Nasal Decongestant

Uses

Temporarily relieves these symptoms due to the common cold, hay fever (allergic rhinitis) or other upper respiratory allergies:

- cough due to minor throat and bronchial irritation
- helps loosen phlegm (mucus) and thin bronchial secretions to drain bronchial tubes and make coughs more productive
- nasal congestion
- reduces swelling of nasal passages

Warnings

Do not exceed recommended dosage.

Do not use this product

- if you are now taking a prescription monoamine oxidase inhibitor (MAOI) (certain drugs for depression, psychiatric, or emotional conditions, or Parkinson’s disease), or for 2 weeks after stopping the MAOI drug. If you do not know if your prescription drug contains an MAOI, ask a doctor or pharmacist before taking this product.

Ask a doctor before use if you have

- a cough that lasts or is chronic such as occurs with smoking, asthma, chronic bronchitis, or emphysema
- a cough that occurs with too much phlegm (mucus)
- heart disease
- high blood pressure
- thyroid disease
- diabetes
- trouble urinating due to enlargement of the prostate gland

Stop use and ask a doctor if:

- nervousness, dizziness, or sleeplessness occur
- cough or nasal congestion persists for more than 1 week, tends to recur, or is accompanied by fever, rash, or persistent headache. A persistent cough may be a sign of a serious condition.
- new symptoms occur

If pregnant or breast feeding,

ask a health professional before use.

Keep out of reach of children.

In case of overdose, get medical help or contact a Poison Control Center right away.

Directions

Do not exceed recommended dosage.
Adults and children 12 years of age and over: | 1 tablet every 4 hours, not to exceed 4 tablets in 24 hours, or as directed by a doctor.
Children 6 to under 12 years of age: | 1/2 tablet every 4 hours, not to exceed 2 tablets in 24 hours, or as directed by a doctor.
Children 2 to under 6 years of age: | Consult a doctor.

Other information

Store at 15°-30°C (59°-86°F).

Capmist DM is a light green, oblong, capsule shaped, scored tablet, debossed “CAP” bisect “DM” on one side and blank on the other.

Contains color additives including FD&C Yellow No. 5 (tartrazine).

Supplied in a tight, light-resistant container with a child-resistant cap.

Inactive ingredients

FD&C Blue #1, FD&C Yellow #5, Magnesium Stearate, Microcrystalline Cellulose, Sodium Starch Glycolate.

PRINCIPAL DISPLAY PANEL

NDC 29978-601-90
CAPMIST DM Tablets
Cough Suppressant ● Expectorant
Nasal Decongestant
90 tablets

PRINCIPAL DISPLAY PANEL

NDC 29978-601-30
CAPMIST DM Tablets
Cough Suppressant ● Expectorant
Nasal Decongestant
3 0 samples